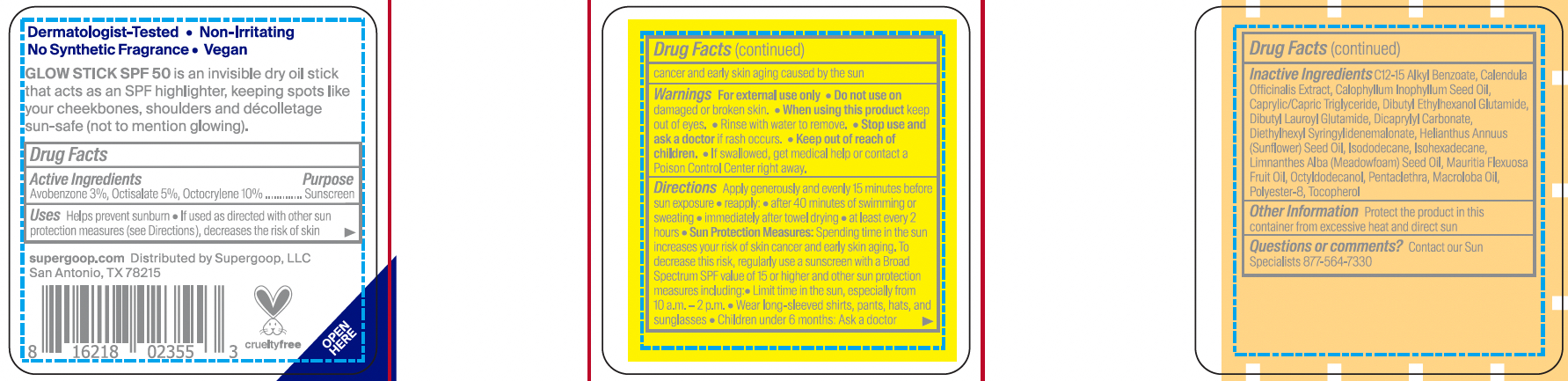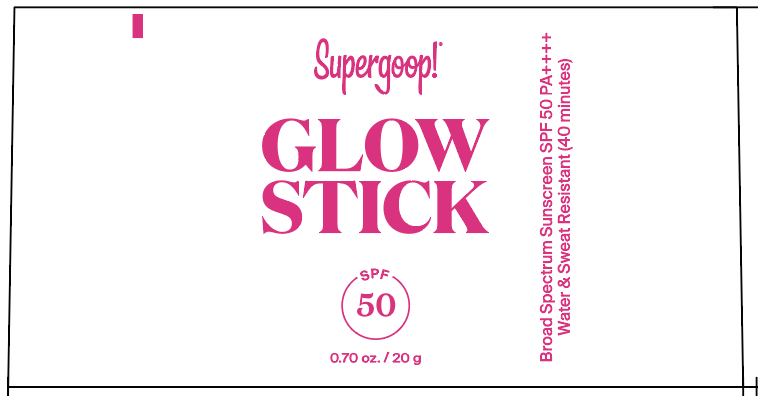 DRUG LABEL: Glow Stick Broad Spectrum SPF 50
NDC: 75936-157 | Form: STICK
Manufacturer: Supergoop, LLC
Category: otc | Type: HUMAN OTC DRUG LABEL
Date: 20231214

ACTIVE INGREDIENTS: OCTISALATE 5 g/100 g; AVOBENZONE 3 g/100 g; OCTOCRYLENE 10 g/100 g
INACTIVE INGREDIENTS: TOCOPHEROL; SUNFLOWER OIL; ISOHEXADECANE; TAMANU OIL; ISODODECANE; ALKYL (C12-15) BENZOATE; DIBUTYL LAUROYL GLUTAMIDE; OCTYLDODECANOL; MEADOWFOAM SEED OIL FATTY ACIDS; CALENDULA OFFICINALIS FLOWER; MEDIUM-CHAIN TRIGLYCERIDES; DICAPRYLYL CARBONATE; POLYESTER-8 (1400 MW, CYANODIPHENYLPROPENOYL CAPPED); DIBUTYL ETHYLHEXANOYL GLUTAMIDE; DIETHYLHEXYL SYRINGYLIDENEMALONATE; PENTACLETHRA MACROLOBA SEED OIL; MAURITIA FLEXUOSA FRUIT OIL

Glow Stick SPF 50

Active Ingredients / Purpose

Avobenzone 3%...... Sunscreen

Octocrylene 10%... Sunscreen

Octisalate 5%.......... Sunscreen

Uses

- Helps prevent sunburn
- If used as directed with other sun protection measures (see Directions), decreases the risk of skin cancer and early skin aging caused by the sun

Keep out of reach of children. If product is swallowed, get medical help or contact a Poison Control Center right away,

Stop use and ask a doctor if rash occurs

Warnings

For external use only

Do not use on damaged or broken skin

When using this product keep out of eyes. Rinse with water to remove.

Directions

- Apply generously and evenly 15 minutes before sun exposure

Reapply:

- After 40 minutes of swimming or sweating
- Immediately after towel drying
- At least every 2 hours

Sun Protection measures Spending time in the sun increases your risk of skin cancer and early skin aging. To decrease this risk, regularly use a sunscreen with a Broad Spectrum SPF value of 15 or higher and other sun protection measures including:

- Limit time in the sun, especially from 10 a.m. - 2 p.m.
- Wear long-sleeved shirts, pants, hats and sunglasses
- Children under 6 months: ask a doctor

Inactive Ingredients

Caprylic/Capric Triglyceride, Octyldodecanol, Isododecane, Isohexadecane, Dicaprylyl Carbonate, C12-15 Alkyl Benzoate, Dibutyl Lauroyl Glutamide, Polyester-8, Dibutyl Ethylhexanoyl Glutamide, Diethylhexyl Syringylidenemalonate, Helianthus Annuus (sunflower) Seed Oil, Pentaclethra Macroloba Seed Oil, Maurita Flexuosa Fruit Oil, Limnanthes Alba (Meadowfoam) Seed Oil, Callophyllum Inophyllum seed Oil, Calendula Officinalis Extract, Tocopherol

RECENT MAJOR CHANGES

Dosage and Administration Section

PACKAGE LABEL

Supergoop! Glow Stick Sunscreen SPF 50

Broad Spectrum Sunscreen SPF 50

1.23 oz./ 35 g